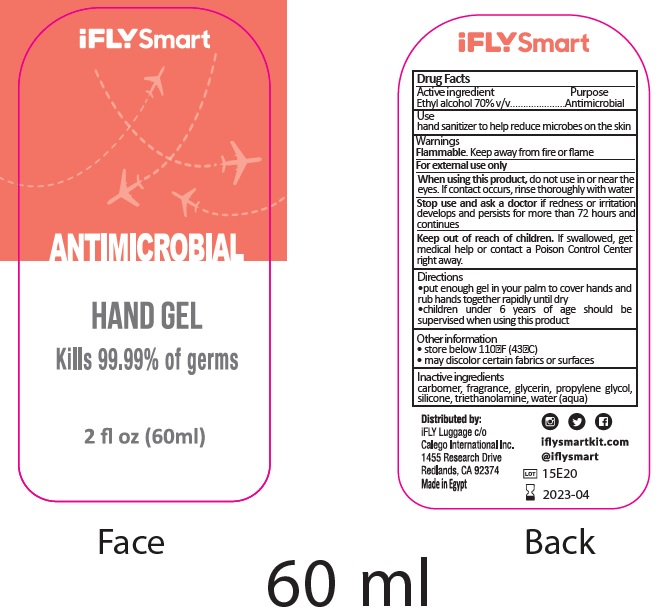 DRUG LABEL: Antimicrobial Hand
NDC: 72487-008 | Form: GEL
Manufacturer: Calego International Inc.
Category: otc | Type: HUMAN OTC DRUG LABEL
Date: 20200514

ACTIVE INGREDIENTS: ALCOHOL 0.7 mL/1 mL
INACTIVE INGREDIENTS: CARBOMER HOMOPOLYMER, UNSPECIFIED TYPE; GLYCERIN; PROPYLENE GLYCOL; TROLAMINE; WATER

Antimicrobial Hand Gel

Active ingredient

Ethyl Alcohol 70% w/w

Purpose

Antimicrobial

Use

hand sanitizer to help reduce microbes on the skin

Warnings

Flammable. Keep away from fire or flame

For external use only.

When using this product,

do not use in or near the eyes. If contact occurs, rinse thoroughly with water

Stop use and ask a doctor

if irritation and redness develops and persists for more than 72 hours and continues

Keep out of reach of children.

If swallowed, get medical help or contact a Poison Control Center right away.

Directions

- put enough gel in your palm to cover hands and rub hands together rapidly until dry
- children under 6 years of age should be supervised when using this product

Other information

- store below 110oF (43oC)
- may discolor certain fabrics or surfaces

Inactive ingredients

carbomer, fragrance, glycerin, propylene glycol, silicone, triethanolamine, water (aqua)